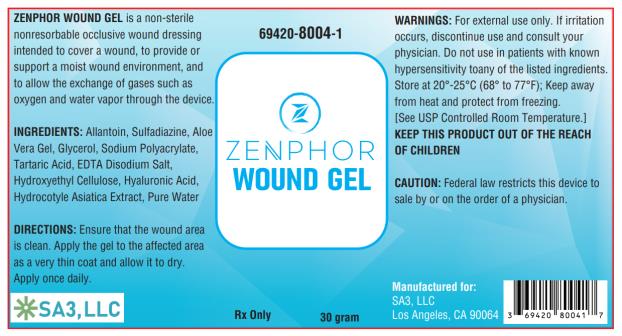 DRUG LABEL: ZENPHOR WOUND
NDC: 71073-211
Manufacturer: Beijing HKKY Medical Tech. Co., Ltd.
Category: other | Type: MEDICAL DEVICE
Date: 20210905

71073-211, Zenphor Wound Gel

Description

ZENPHOR WOUNDGEL is a non-sterile nonresorbable occlusive wound dressing intended to cover a wound, to provide or support a moist wound environment, and to allow the exchange of gases such as oxygen and water vapor through the device.

ZENPHOR WOUNDGELis a self-drying, flexible, gas permeable, gel that is colorless and odorless. It is intended to provide a moist wound healing environment to facilitate the normal wound healing process.

INGREDIENTS

ZENPHOR WOUNDGEL contains: Allantoin, Sulfadiazine, Aloe Vera Gel, Glycerol, Sodium Polyacrylate, Tartaric Acid, EDTA Disodium Salt, Hydroxyethyl Cellulose, Hyaluronic Acid, Hydrocotyle Asiatica Extract, and Pure Water.

INDICATIONS AND USES

It is intended to provide a moist wound healing environment to facilitate the normal wound healing process.

Contraindications

ZENPHOR WOUNDGEL is contraindicated in patients with known hypersensitivity to any of the listed ingredients.

Warnings

For external use only. If irritation occurs, discontinue use and consult your physician. Do not use in patients with known hypersensitivity to any of the listed ingredients. Store at 20°-25°C (68° to 77°F); Keep away from heat and protect from freezing. [See USP Controlled Room Temperature.]

KEEP THIS PRODUCT OUT OF THE REACH OF CHILDREN

Precautions

Stop use and ask a doctor if irritation develops. In rare instances, silicone sheets may cause a rash on the skin. If ingested, get medical help or contact Poison Control Center right away.
This medication should be used as directed by your physician during pregnancy or while breastfeeding. Consult your doctor about the risks and benefits.
CAUTION: Federal law restricts this device to sale by or on the order of a physician.

Adverse Reactions

On rare occasions, the gel may cause temporary redness, stinging, burning or irritation and normally disappear when the medication is discontinued.

Dosage and Administration

Ensure that the wound area is clean. Apply the gel to the affected area as a very thin coat and allow it to dry. Apply once daily.

How is ZENPHOR WOUNDGEL Supplied

ZENPHOR WOUNDGEL is supplied in:
30 gram bottle
69420-8004-1

Store at 20°-25°C (68° to 77°F); Keep away from heat and protect from freezing. [See USP Controlled Room Temperature.]
Manufactured for:
SA3, LLC
Los Angeles, CA 90064